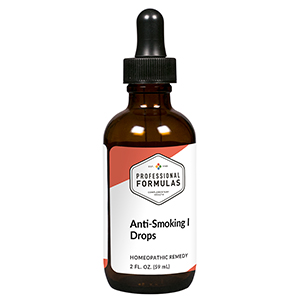 DRUG LABEL: Anti-Smoking I Drops
NDC: 63083-2007 | Form: LIQUID
Manufacturer: Professional Complementary Health Formulas
Category: homeopathic | Type: HUMAN OTC DRUG LABEL
Date: 20190815

ACTIVE INGREDIENTS: TOBACCO LEAF 4 [hp_X]/59 mL; SUS SCROFA ADRENAL GLAND 6 [hp_X]/59 mL; LOBELIA CARDINALIS WHOLE 6 [hp_X]/59 mL; BEEF LUNG 6 [hp_X]/59 mL; NICOTINE 6 [hp_X]/59 mL; BETA-ENDORPHIN HUMAN 6 [hp_X]/59 mL; COFFEA ARABICA SEED, ROASTED 6 [hp_X]/59 mL; STRYCHNOS NUX-VOMICA SEED 12 [hp_X]/59 mL; SUCROSE 16 [hp_X]/59 mL
INACTIVE INGREDIENTS: ALCOHOL; WATER

C7

ACTIVE INGREDIENTS

Tabacum 4X, 12X, 30X, 100X
Adrenal 6X
Lobelia cardinalis 6X
Lung 6X
Nicotinum 6X
Endorphins 6X, 30X
Coffea tosta 6X, 30X, 100X
Nux vomica 12X
Saccharum officinale 16X, 60X

QUESTIONS

Professional Formulas

PO Box 2034 Lake Oswego, OR 97035

INDICATIONS

Temporarily reduces cravings while attempting to quit smoking.*

PURPOSE

*Claims based on traditional homeopathic practice, not accepted medical evidence. Not FDA evaluated.

WARNINGS

In case of overdose, get medical help or contact a poison control center right away.

Keep out of the reach of children.

PREGNANCY OR BREAST FEEDING

If pregnant or breastfeeding, ask a healthcare professional before use.

DIRECTIONS

Place drops under tongue 30 minutes before/after meals. Adults and children 12 years and over: Take 10 drops up to 3 times per day. Consult a physician for use in children under 12 years of age.

OTHER INFORMATION

Tamper resistant. If seal is broken, do not use. After opening, close container tightly and store at room temperature away from heat.

INACTIVE INGREDIENTS

20% ethanol, purified water.

LABEL

Est 1985

Professional Formulas

Complementary Health

Anti-Smoking I Drops

Homeopathic Remedy

2 FL. OZ. (59 mL)